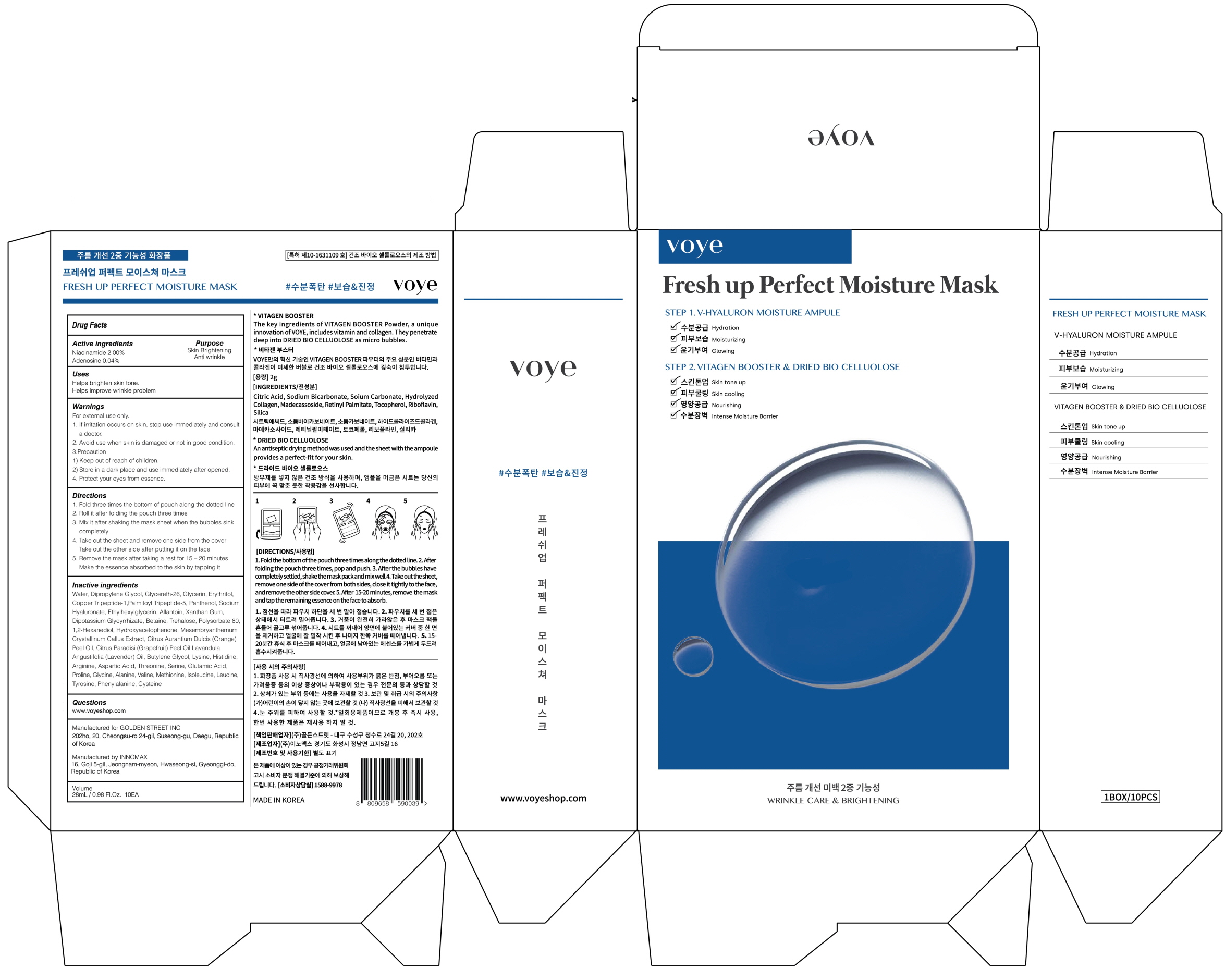 DRUG LABEL: Voye Fresh Up Perfect Moisture Mask V Hyaluron Moisture Ampule
NDC: 73265-030 | Form: PATCH
Manufacturer: Golden Street
Category: otc | Type: HUMAN OTC DRUG LABEL
Date: 20190801

ACTIVE INGREDIENTS: Niacinamide 0.56 g/28 mL; Adenosine 0.01 g/28 mL
INACTIVE INGREDIENTS: Water; Dipropylene Glycol

ACTIVE INGREDIENT

Active Ingredients: Niacinamide 2.00%, Adenosine 0.04%

INACTIVE INGREDIENT

Inactive ingredients:
Water, Dipropylene Glycol, Glycereth-26, Glycerin, Erythritol, Copper Tripeptide-1,Palmitoyl Tripeptide-5, Panthenol, Sodium Hyaluronate, Ethylhexylglycerin, Allantoin, Xanthan Gum, Dipotassium Glycyrrhizate, Betaine, Trehalose, Polysorbate 80, 1,2-Hexanediol, Hydroxyacetophenone, Mesembryanthemum Crystallinum Callus Extract, Citrus Aurantium Dulcis (Orange) Peel Oil, Citrus Paradisi (Grapefruit) Peel Oil Lavandula Angustifolia (Lavender) Oil, Butylene Glycol, Lysine, Histidine, Arginine, Aspartic Acid, Threonine, Serine, Glutamic Acid, Proline, Glycine, Alanine, Valine, Methionine, Isoleucine, Leucine, Tyrosine, Phenylalanine, Cysteine

PURPOSE

Purpose: Skin Brightening, Anti wrinkle

WARNINGS

For external use only.
1. If irritation occurs on skin, stop use immediately and consult a doctor.
2. Avoid use when skin is damaged or not in good condition.
3.Precaution
1) Keep out of reach of children.
2) Store in a dark place and use immediately after opened.
4. Protect your eyes from essence.

KEEP OUT OF REACH OF CHILDREN

Uses

Helps brighten skin tone.
Helps improve wrinkle problem.

Directions

1. Fold three times the bottom of pouch along the dotted line
2. Roll it after folding the pouch three times
3. Mix it after shaking the mask sheet when the bubbles sink completely
4. Take out the sheet and remove one side from the cover
Take out the other side after putting it on the face
5. Remove the mask after taking a rest for 15 – 20 minutes
Make the essence absorbed to the skin by tapping it.